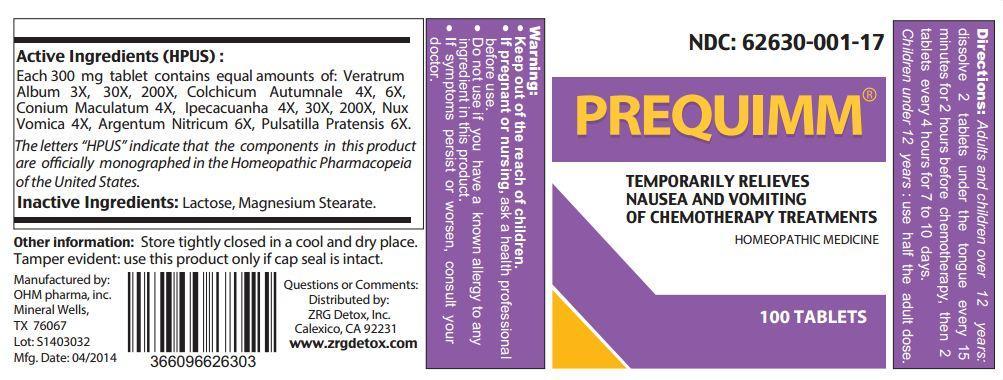 DRUG LABEL: PREQUIMM
                
NDC: 62630-001 | Form: TABLET, ORALLY DISINTEGRATING
Manufacturer: ZRG DETOX, INC.
Category: homeopathic | Type: HUMAN OTC DRUG LABEL
Date: 20190909

ACTIVE INGREDIENTS: VERATRUM ALBUM ROOT 3 [hp_X]/1 1; COLCHICUM AUTUMNALE BULB 4 [hp_X]/1 1; CONIUM MACULATUM FLOWERING TOP 4 [hp_X]/1 1; IPECAC 4 [hp_X]/1 1; STRYCHNOS NUX-VOMICA SEED 4 [hp_X]/1 1; SILVER NITRATE 6 [hp_X]/1 1; PULSATILLA PRATENSIS 6 [hp_X]/1 1
INACTIVE INGREDIENTS: LACTOSE MONOHYDRATE; MAGNESIUM STEARATE

PREQUIMM

Active Ingredients (HPUS):

Each 300 mg tablet contains equal amounts of: Veratrum Album 3X, 30X, 200X, Colchicum Autumnale 4X, 6X, Conium Maculatum 4X, Ipecacuanha 4X, 30X, 200X, Nux Vomica 4X, Argentum Nitricum 6X, Pulsatila Pratensis 6X.

OTHER SAFETY INFORMATION

The letters "HPUS" indicate that the components in this product are officially monographed in the Homeopathic Pharmacopeia of the United States.

Inactive Ingredients: Lactose, Magnesium Stearate.

Directions:

- Adults and children over 12 years: dissolve 2 tablets under the tongue every 15 minutes for 2 hours before chemotherapy, then 2 tablets every 4 hours for 7 to 10 days.
- Children under 12 years: use half the adult dose.

Warning:

- Keep out of the reach of children.
- If pregnant or nursing, ask a health professional before use.
- Do not use if you have a known allergy to any ingredient in this product.
- If symptoms persist or worsen, consult your doctor.

Keep out of the reach of children.

INDICATIONS AND USAGE

Temporarily relieves nasea and vomiting of chemotherapy treatments.

Other information: Store tightly closed in a cool and dry place. Tamper evident: use this product only if cap seal is intact.

Questions or Comments:

Distributed by: ZRG Detox, Inc.

Calexico, CA 92231

www.zrgdetox.com

OTHER SAFETY INFORMATION

Manufactured by:

OHM pharma, inc.

Mineral Wells, TX 76067

PACKAGE LABEL

NDC: 62630-001-17

PREQUIMM

HOMEOPATHIC MEDICINE

100 TABLETS

PURPOSE

TEMPORARILY RELIEVES NAUSEA AND VOMITING OF CHEMOTHERAPY TREATMENTS.